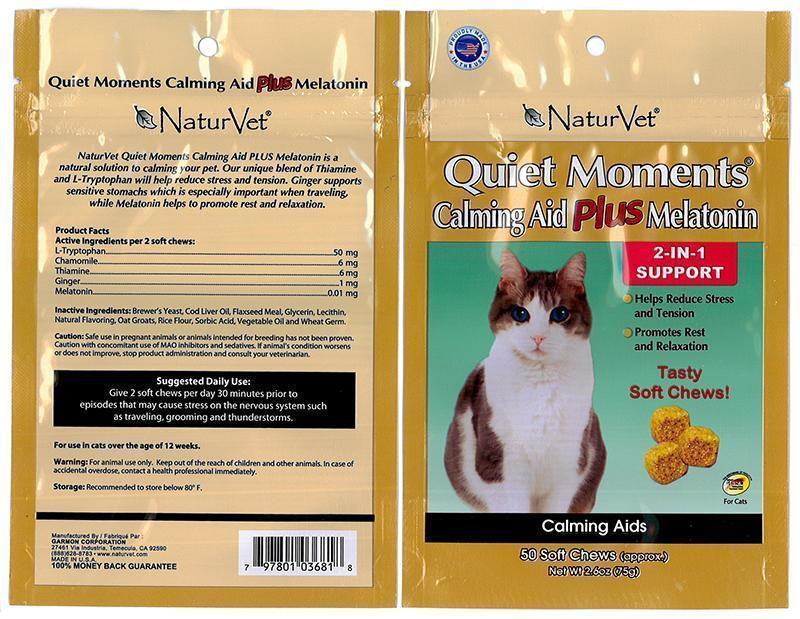 DRUG LABEL: Quiet Moments Calming Aid Plus Melatonin
NDC: 27135-0368 | Form: BAR, CHEWABLE
Manufacturer: The Garmon Corporation
Category: animal | Type: OTC ANIMAL DRUG LABEL
Date: 20140121

ACTIVE INGREDIENTS: TRYPTOPHAN 50 mg/1 1; CHAMOMILE 6 mg/1 1; THIAMINE 6 mg/1 1; GINGER 1 mg/1 1; MELATONIN 0.01 mg/1 1

NaturVet Quiet Moments Calming Aid Plus Melatonin

Product Facts

Active Ingredients per 2 soft chews:

L-Tryptophan………………………50 mg

Chamomile…………………………..6 mg

Thiamine Mononitrate…………6 mg

Ginger………………………………….1 mg

Melatonin……………………….0.01 mg

INACTIVE INGREDIENT

Inactive Ingredients: Brewer’s Dried Yeast, Cod Liver Oil, Flaxseed Meal, Glycerin, Lecithin, Natural Flavoring, Oat Groats, Rice Flour, Sorbic Acid, Vegetable Oil and Wheat Germ.

PRECAUTIONS

Caution: Safe use in pregnant animals or animals intended for breeding has not been proven. Caution with concomitant use of MAO Inhibitors and sedatives. If animal’s condition worsens or does not improve, stop product administration and consult your veterinarian.

DOSAGE AND ADMINISTRATION

Suggested Daily Use: Give 2 soft chews per day 30 minutes prior to episodes that may cause stress on the nervous system such as traveling, grooming and thunderstorms. For use in cats over the age of 12 weeks.

WARNINGS

Warning: For animal use only. Keep out of reach of children and other animals. In case of accidental overdose, consult health professional immediately.

Storage: Recommended to store below 80°F.